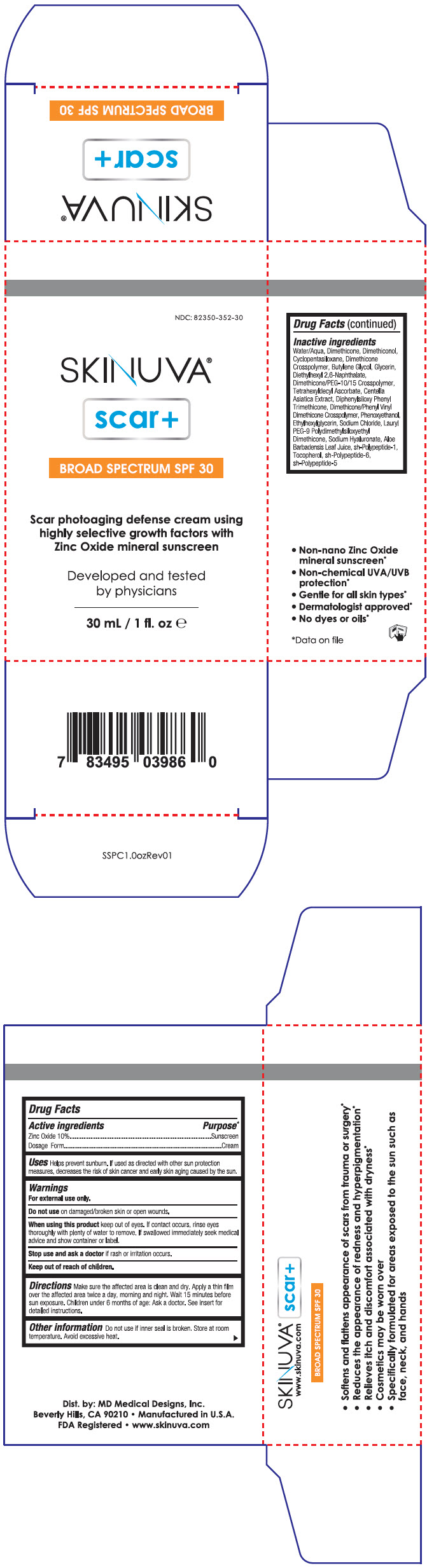 DRUG LABEL: Skinuva Scar plus
NDC: 82350-352 | Form: CREAM
Manufacturer: MD Medical Designs, Inc.
Category: otc | Type: HUMAN OTC DRUG LABEL
Date: 20250725

ACTIVE INGREDIENTS: ZINC OXIDE 0.1 g/1 mL
INACTIVE INGREDIENTS: WATER; DIMETHICONE, UNSPECIFIED; CYCLOMETHICONE 5; BUTYLENE GLYCOL; GLYCERIN; DIETHYLHEXYL 2,6-NAPHTHALATE; DIMETHICONE/PEG-10/15 CROSSPOLYMER; TETRAHEXYLDECYL ASCORBATE; CENTELLA ASIATICA TRITERPENOIDS; DIPHENYLSILOXY PHENYL TRIMETHICONE; DIMETHICONE/PHENYL VINYL DIMETHICONE CROSSPOLYMER; ETHYLHEXYLGLYCERIN; SODIUM CHLORIDE; LAURYL PEG-9 POLYDIMETHYLSILOXYETHYL DIMETHICONE; HYALURONATE SODIUM; ALOE VERA LEAF; BASIC FIBROBLAST GROWTH FACTOR (HUMAN); TOCOPHEROL; PHENOXYETHANOL; INTERLEUKIN-10

Skinuva® Scar plus

Drug Facts

ACTIVE INGREDIENT

Active ingredients | Purpose [Data on file]
Zinc Oxide 10% | Sunscreen
Dosage Form | Cream

Uses

Helps prevent sunburn. If used as directed with other sun protection measures, decreases the risk of skin cancer and early skin aging caused by the sun.

Warnings

For external use only.

Do not use on damaged/broken skin or open wounds.

When using this product keep out of eyes. If contact occurs, rinse eyes thoroughly with plenty of water to remove. If swallowed immediately seek medical advice and show container or label.

Stop use and ask a doctor if rash or irritation occurs.

Keep out of reach of children.

Directions

Make sure the affected area is clean and dry. Apply a thin film over the affected area twice a day, morning and night. Wait 15 minutes before sun exposure. Children under 6 months of age: Ask a doctor. See insert for detailed instructions.

Other information

Do not use if inner seal is broken. Store at room temperature. Avoid excessive heat.

Inactive ingredients

Water/Aqua, Dimethicone, Dimethiconol, Cyclopentasiloxane, Dimethicone Crosspolymer, Butylene Glycol, Glycerin, Diethylhexyl 2,6-Naphthalate, Dimethicone/PEG-10/15 Crosspolymer, Tetrahexyldecyl Ascorbate, Centella Asiatica Extract, Diphenylsiloxy Phenyl Trimethicone, Dimethicone/Phenyl Vinyl Dimethicone Crosspolymer, Phenoxyethanol, Ethylhexylglycerin, Sodium Chloride, Lauryl PEG-9 Polydimethylsiloxyethyl Dimethicone, Sodium Hyaluronate, Aloe Barbadensis Leaf Juice, sh-Polypeptide-1, Tocopherol, sh-Polypeptide-6, sh-Polypeptide-5

Dist. by: MD Medical Designs, Inc.
Beverly Hills, CA 90210

PRINCIPAL DISPLAY PANEL - 30 mL Bottle Carton

NDC: 82350-352-30

SKINUVA®
scar+

BROAD SPECTRUM SPF 30

Scar photoaging defense cream using
highly selective growth factors with
Zinc Oxide mineral sunscreen

Developed and tested
by physicians

30 mL / 1 fl. oz e